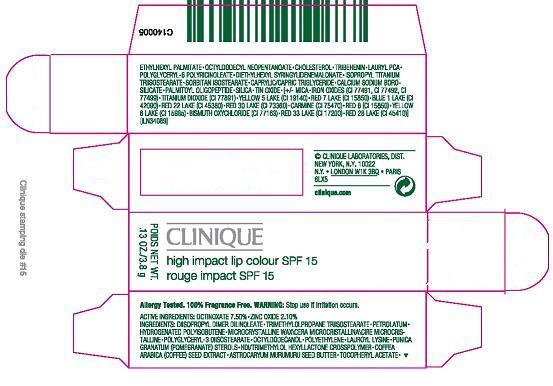 DRUG LABEL: HIGH IMPACT LIP COLOUR 
NDC: 49527-727 | Form: CREAM
Manufacturer: CLINIQUE LABORATORIES INC
Category: otc | Type: HUMAN OTC DRUG LABEL
Date: 20100419

ACTIVE INGREDIENTS: OCTINOXATE  7.5 g/100 g; ZINC OXIDE 2.1 g/100 g

ACTIVE INGREDIENT

ACTIVE INGREDIENTS: OCTINOXATE 7.50% [] ZINC OXIDE 2.10%

WARNINGS

WARNING: STOP USE IF IRRITATION OCCURS

PACKAGE LABEL

PRINCIPAL DISPLAY PANEL:

CLINIQUE

HIGH IMPACT LIP COLOUR SPF 15

NET WT.
0.13 OZ / 3.8 G
CLINIQUE LABORTORIES, DIST.
NEW YORK, NY 10022